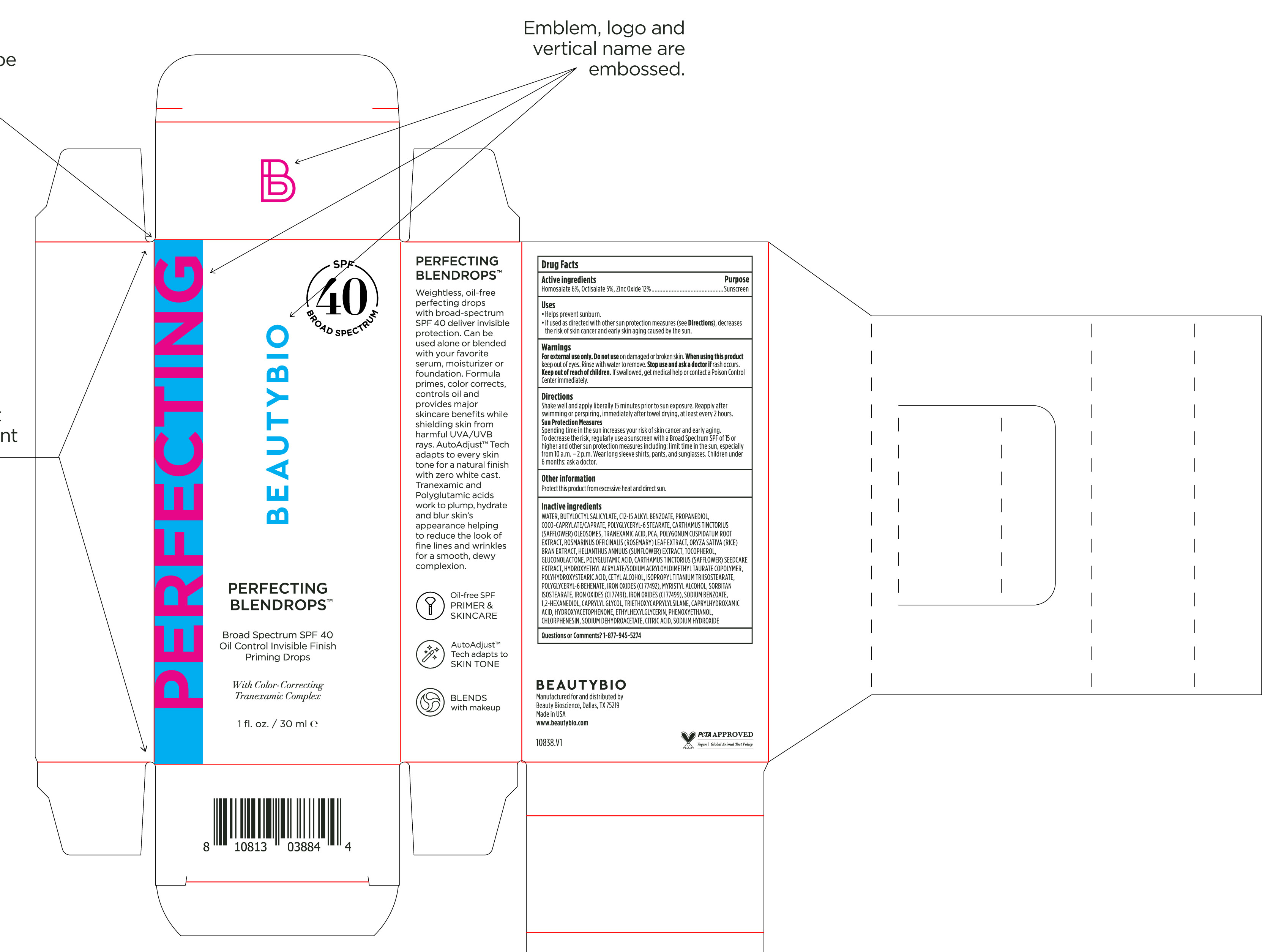 DRUG LABEL: Perfecting Blendrops Broad Spectrum SPF 40
NDC: 44717-084 | Form: SOLUTION/ DROPS
Manufacturer: Wasatch Product Development, LLC
Category: otc | Type: HUMAN OTC DRUG LABEL
Date: 20251209

ACTIVE INGREDIENTS: ZINC OXIDE 12 g/100 mL; HOMOSALATE 6 g/100 mL; OCTISALATE 5 g/100 mL
INACTIVE INGREDIENTS: RICE BRAN; GLUCONOLACTONE; CHLORPHENESIN; WATER; ROSEMARY; SORBITAN ISOSTEARATE; SODIUM DEHYDROACETATE; CITRIC ACID MONOHYDRATE; SODIUM HYDROXIDE; ALKYL (C12-15) BENZOATE; TOCOPHEROL; COCO-CAPRYLATE/CAPRATE; CAPRYLHYDROXAMIC ACID; PHENOXYETHANOL; FERRIC OXIDE RED; FERRIC OXIDE YELLOW; BUTYLOCTYL SALICYLATE; HYDROXYETHYL ACRYLATE/SODIUM ACRYLOYLDIMETHYL TAURATE COPOLYMER (45000 MPA.S AT 1%); ISOPROPYL TITANIUM TRIISOSTEARATE; MYRISTYL ALCOHOL; CARTHAMUS TINCTORIUS SEEDCAKE; CARTHAMUS TINCTORIUS (SAFFLOWER) OLEOSOMES; PIDOLIC ACID; HELIANTHUS ANNUUS FLOWERING TOP; CETYL ALCOHOL; FERROSOFERRIC OXIDE; PROPANEDIOL; SODIUM BENZOATE; HYDROXYACETOPHENONE; POLYGLYCERYL-6 BEHENATE; TRIETHOXYCAPRYLYLSILANE; TRANEXAMIC ACID; POLYGLYCERYL-6 STEARATE; POLYGONUM CUSPIDATUM ROOT; POLYHYDROXYSTEARIC ACID (2300 MW); 1,2-HEXANEDIOL; CAPRYLYL GLYCOL; ETHYLHEXYLGLYCERIN

Perfecting Blendrops Broad Spectrum SPF 40

Active ingredients Purpose

Homosalate 6%, Octisalate 5%, Zinc Oxide 12% ......... Suncreen

Uses

- Helps prevent sunburn.
- If used as directed with other sun protection measures (see Directions), drecreases the risk of skin cancer and early skin aging caused by the sun.

Keep out of reach of children. If swallowed, get medical help or contact a Poison Control Center immediately.

Stop use and ask a doctor if rash occurs.

WARNINGS

fskdjfsd

Directions

Shake well and apply liberally 15 minutes prior to sun exposure. Reapply after swimmng or perspiring, immediately after towel drying, at least every 2 hours.

Sun Protection Measures

Spending time in the sun increases your risk of skin cancer and early aging. To decrease the risk, regularly use a sunscreen with a Broad Spectrum SPF of 15 or higher and other sun protection measures including: limit time in the sun, especially from 10 a.m.- 2p.m. Wear long sleeve shirts, pants, and sunglases. Children under 6 months: ask a doctor,.

Other information

Protect this product from excessive heat and direct sun.

Inactive ingredients

Water, Butyloctyl Salicylate, C12-15 Alkyl Benzoate, Propanediol, Coco-Caprylate/Caprate, Polyglyceryl-6 Stearate, Carthamus Tinctorius (Safflower) Oleosomes, Tranexamic Acid, PCA, Polygonum Cuspidatum Root Extract, Rosmarinus Officinalis (Rosemary) Leaf Extract, Oryza Sativa (Rice) Bran Extract, Helianthus Annuus (Sunflower) Extract, Tocopherol, Gluconolactone, Polyglytamic Acid, Carthamus Tinctorius (Safflower) Seedcake Extract, Hydroxyethyl Acryleta/Sodium Acryloyldimethyl Taurate Copolymer, Polyhydroxystearic Acid, Cetyl Alcohol, Isopropryl Titanium Triisostearate, Polyglyceryl-6 Behenate, Iron Oxides (CI 77492), Myristyl Alcohol, Sorbitan Isostearate, Iron Oxides (CI 77491), Iron Oxides (CI 77499), Sodium Benzoate, 1,2-Hexanediol, Caprylyl Glycol, Triethoxycaprylylsilane, Caprylhydroxamic Acid, Hydroxyacetophenone, Ethylhexylglycerin, Phenoxyethanol, Chlorphenesin, Sodium Dehydroacetate, Citric Acid, Sodium Hydroxide.

QUESTIONS

Question or comments? 1-877-945-5274

PACKAGE LABEL

PERFECTING

BEAUTYBIO

PERFECTING BLENDROPS

Broad Spectrum SPF 40

Oil Control Invisible Finish Priming Drops

With Color-Correcting Tranexamic Complex

1 fl. oz./ 30 ml